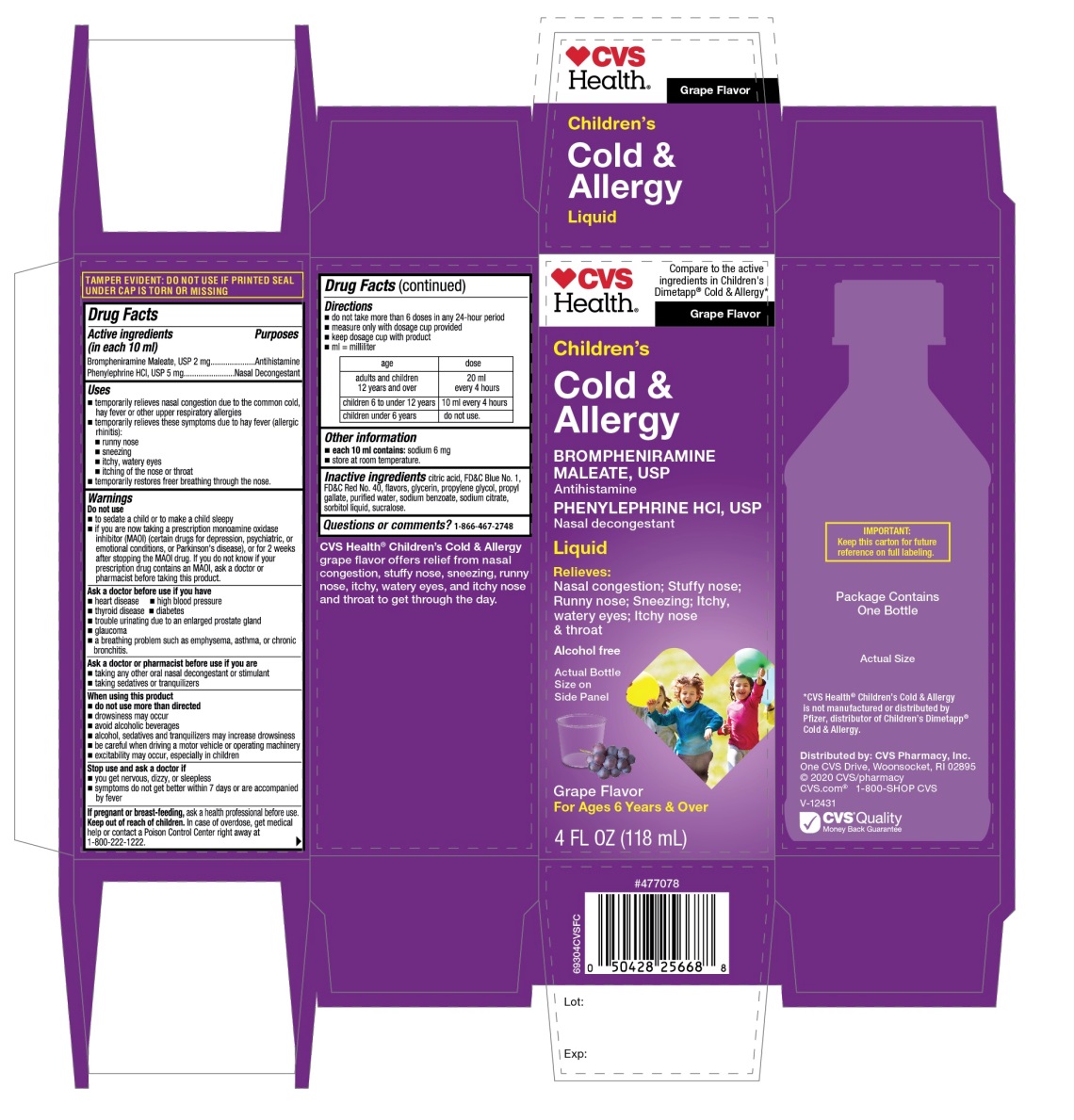 DRUG LABEL: CVS Childrens Cold and Allergy
NDC: 69842-639 | Form: LIQUID
Manufacturer: CVS PHARMACY, INC.
Category: otc | Type: HUMAN OTC DRUG LABEL
Date: 20251209

ACTIVE INGREDIENTS: BROMPHENIRAMINE MALEATE 2 mg/10 mL; PHENYLEPHRINE HYDROCHLORIDE 5 mg/10 mL
INACTIVE INGREDIENTS: ANHYDROUS CITRIC ACID; FD&C BLUE NO. 1; FD&C RED NO. 40; GLYCERIN; PROPYLENE GLYCOL; PROPYL GALLATE; WATER; SODIUM BENZOATE; SODIUM CITRATE, UNSPECIFIED FORM; SORBITOL; SUCRALOSE

Children's Dimetapp Cold & Allergy Brompheniramine maleate and Phenylephrine HCl

Active Ingredients (in each 10 mL)

Brompheniramine maleate, USP 2 mg

Phenylephrine HCl, USP 5 mg

PURPOSES

Antihistamine

Nasal Decongestant

USES

- temporarily relieves nasal congestion due to the common cold, hay fever or other upper respiratory allergies
- temporarily relieves these symptoms due to hay fever (allergic rhinitis):
  - runny nose
  - sneezing
  - itchy, watery eyes
  - itching of the nose or throat
- temporarily restores freer breathing through the nose

WARNINGS

Do not use

- to sedate a child or to make a child sleepy
- if you are now taking a prescription monoamine oxidase inhibitor (MAOI) (certain drugs for depression, psychiatric, or emotional conditions, or Parkinson's disease), or for 2 weeks after stopping the MAOI drug. If you do not know if your prescription drug contains an MAOI, ask a doctor or pharmacist before taking this product.

Ask a doctor before use if you have

- heart disease
- high blood pressure
- thyroid disease
- diabetes
- trouble urinating due to an enlarged prostate gland
- glaucoma
- a breathing problem such as emphysema, asthma, or chronic bronchitis

Ask a doctor or pharmacist before use if you are

- taking any other oral nasal decongestant or stimulant
- taking sedatives or tranquilizers

When using this product

- do not use more than directed
- drowsiness may occur
- avoid alcoholic beverages
- alcohol, sedatives, and tranquilizers may increase drowsiness
- be careful when driving a motor vehicle or operating machinery
- excitability may occur, especially in children

Stop use and ask a doctor if

- you get nervous, dizzy, or sleepless
- symptoms do not get better within 7 days or are accompanied by fever

If pregnant or breast-feeding,

ask a health professional before use.

Keep out of reach of children.

In case of overdose, get medical help or contact a Poison Control Center right away at 1-800-222-1222.

DIRECTIONS

- do not take more than 6 doses in any 24-hour period
- measure only with dosage cup provided
- keep dosage cup with product
- ml = milliliter

age | Dose
adults and children 12 years and over | 20 ml every 4 hours
children 6 to under 12 years | 10 ml every 4 hours
children under 6 years | do not use

OTHER INFORMATION

- each 10 ml contains:sodium 6 mg
- store at room temperature

INACTIVE INGREDIENTS

anhydrous citric acid, FD&C Blue No. 1, FD&C Red No. 40, flavor, glycerin, propylene glycol, propyl gallate, purified water, sodium benzoate, sodium citrate, sorbitol liquid, sucralose

Questions or comments?

1-866-467-2748

PRINCIPAL DISPLAY PANEL - 118 ml Bottle Label

Compare to the active ingredients in Children’s Dimetapp® Cold & Allergy*

NDC# 69842-639-04

Children's Cold& Allergy

Brompheniramine Maleate USP (Antihistamine)
Phenylephrine HCl USP (Nasal Decongestant)

- Stuffy Nose
- Runny Nose
- Sneezing
- Itchy, Watery Eyes

Alcohol-Free • Sugar Free

Ages 6 Years and Over

Grape Flavor

Naturally and Artificially Flavored

4 FL OZ (118 ml)

IMPORTANT:Keep this carton for future reference on full labeling.

Distributed by:

CVS Pharmacy, Inc.

One CVS Drive, Woonsocket, RI 02895

© 2020 CVS/pharmacy

CVS.com 1-800-SHOP CVS

V12431

CVS Quality

Money Back Guaranteed

*This product is not manufactured or distributed by Pfizer, the distributor of Children’s Dimetapp® Cold & Allergy.